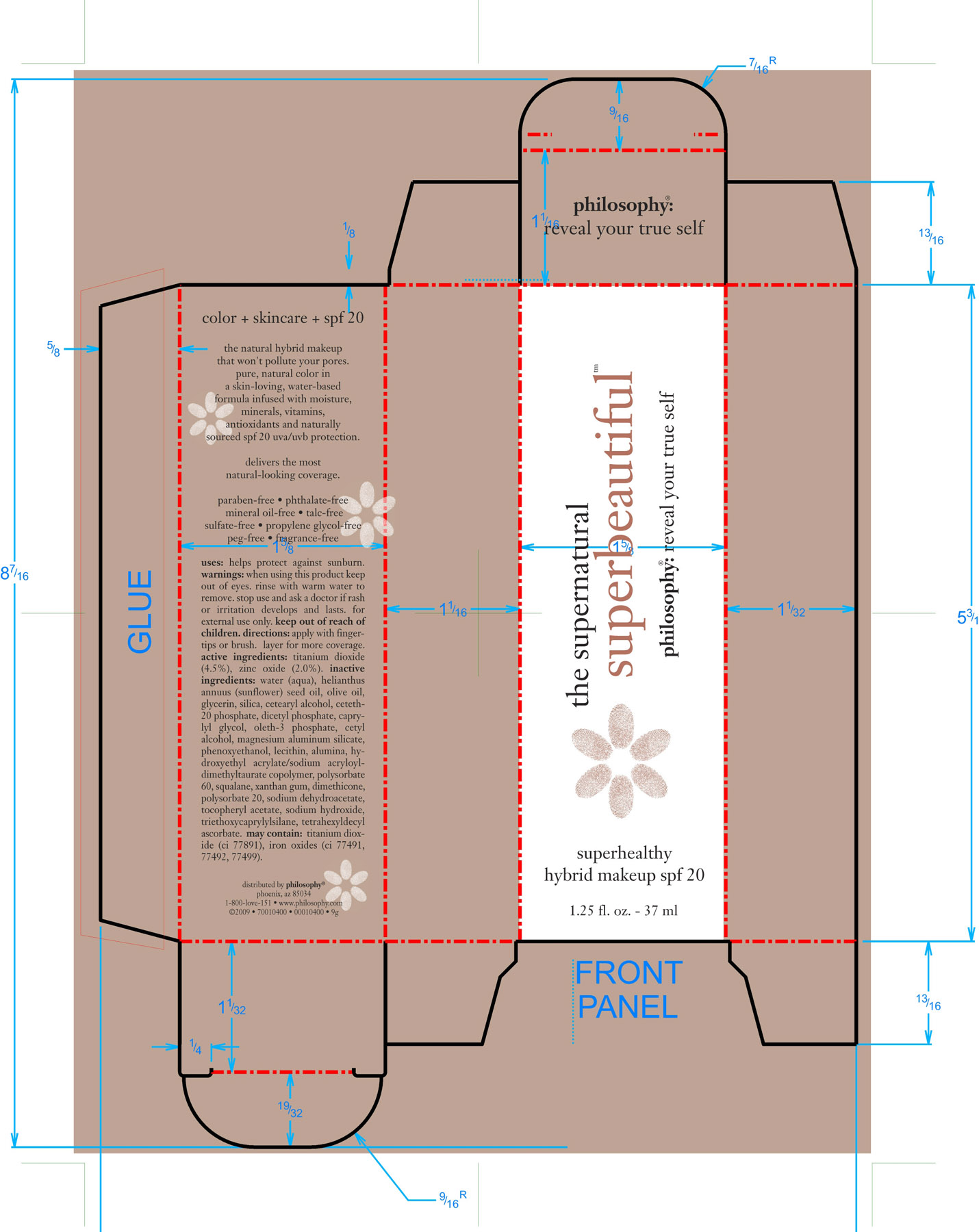 DRUG LABEL: Supernatural Superbeautiful Makeup SPF 15
NDC: 50184-6000 | Form: CREAM
Manufacturer: Philosophy, Inc.
Category: otc | Type: HUMAN OTC DRUG LABEL
Date: 20100123

ACTIVE INGREDIENTS: Titanium Dioxide 45 mg/1 g; Zinc Oxide 20 mg/1 g
INACTIVE INGREDIENTS: Water; HELIANTHUS ANNUUS; OLIVE OIL; GLYCERIN; SILICON DIOXIDE; CETOSTEARYL ALCOHOL; Ceteth-20; DIHEXADECYL PHOSPHATE; CAPRYLYL GLYCOL; OLETH-3 PHOSPHATE; CETYL ALCOHOL; MAGNESIUM ALUMINUM SILICATE; PHENOXYETHANOL; EGG PHOSPHOLIPIDS; ALUMINUM OXIDE; POLYSORBATE 60; SQUALANE; XANTHAN GUM; DIMETHICONE; POLYSORBATE 20; SODIUM DEHYDROACETATE; .ALPHA.-TOCOPHEROL ACETATE, D-; SODIUM HYDROXIDE; OCTYLTRIETHOXYSILANE; TETRAHEXYLDECYL ASCORBATE; TITANIUM DIOXIDE; FERRIC OXIDE RED ; FERRIC OXIDE YELLOW ; FERROSOFERRIC OXIDE

DRUG FACTS

ACTIVE INGREDIENTS......

TITANIUM DIOXIDE (4.5%)

ZINC OXIDE (2.0%)

STOP USE AND ASK DOCTOR IF RASH OR IRRITATION DEVELOPS AND LASTS.

KEEP OUT OF REACH OF CHILDREN. FOR EXTERNAL USE ONLY

WHEN USING THIS PRODUCT KEEP OUT OF EYES. RINSE WITH WARM WATER TO REMOVE.

INDICATIONS AND USAGE

Uses: helps protect against sunburn.

Directions: apply with fingertips or brush, layer for more coverage.